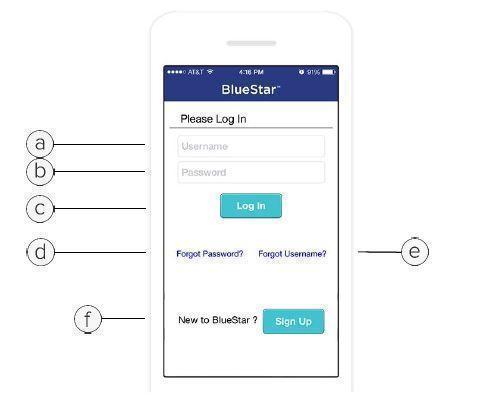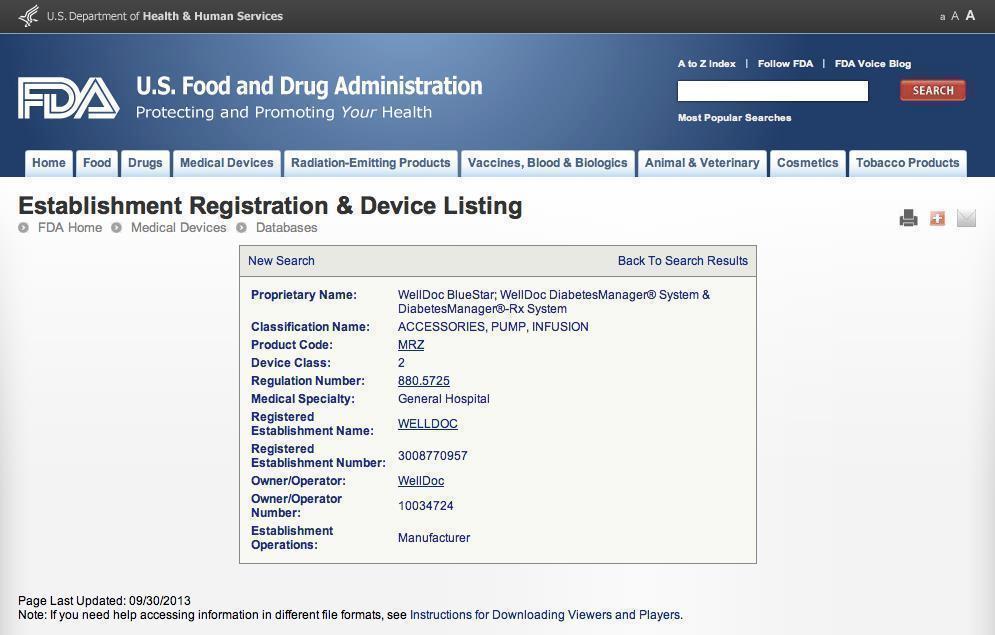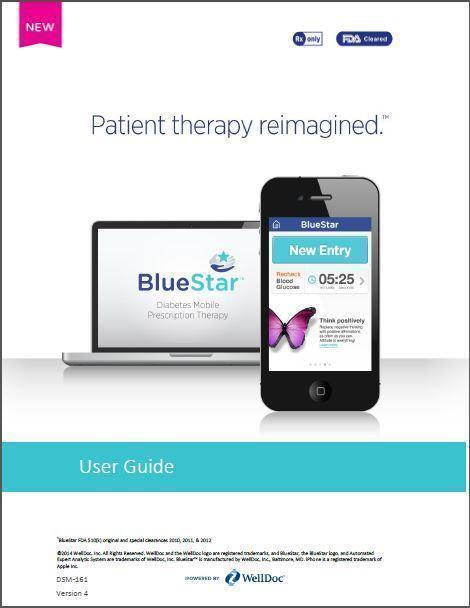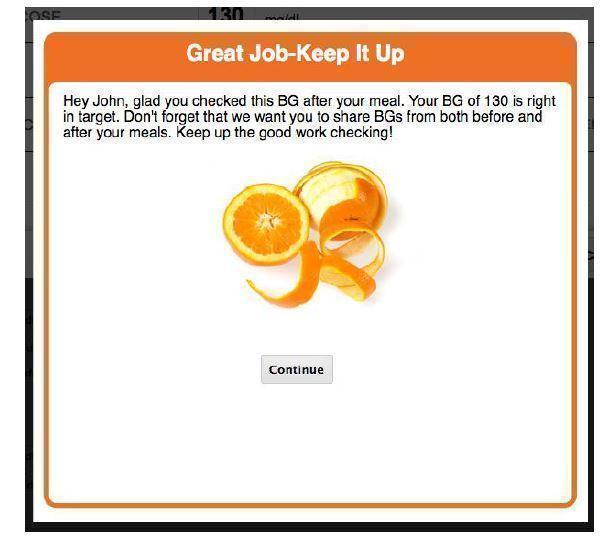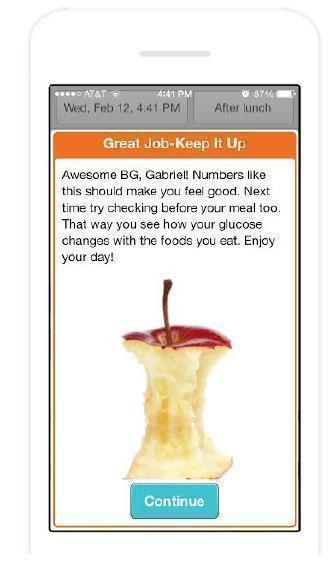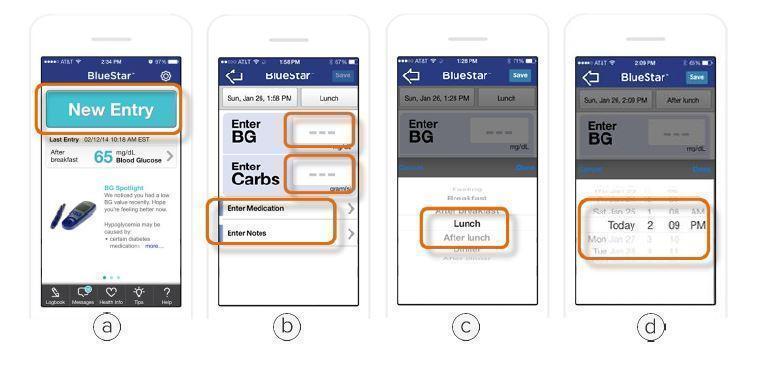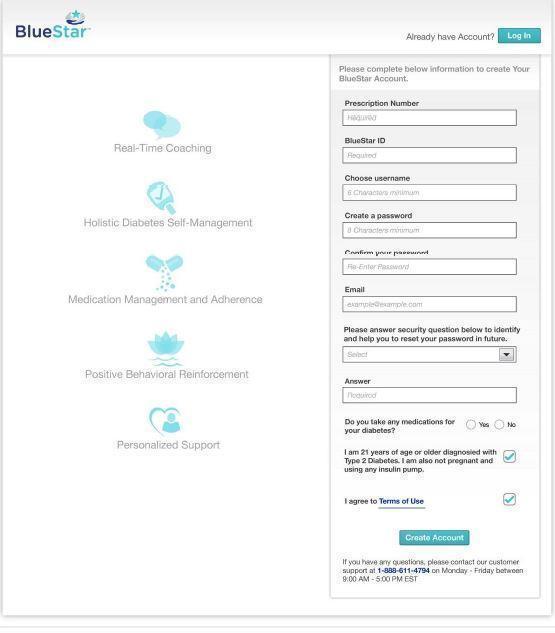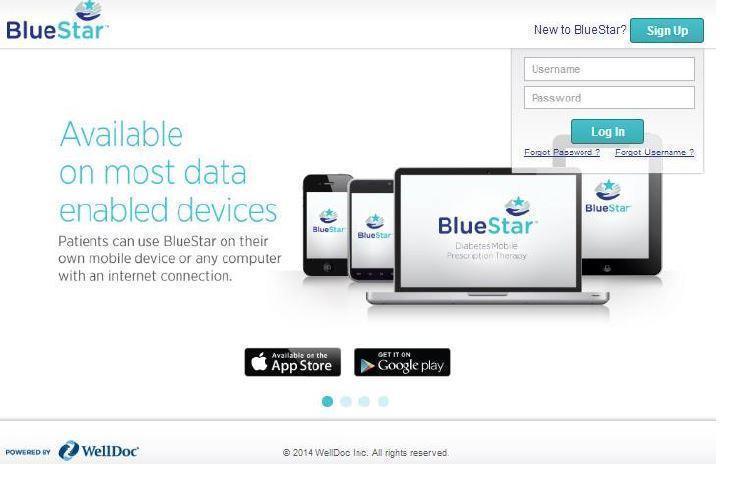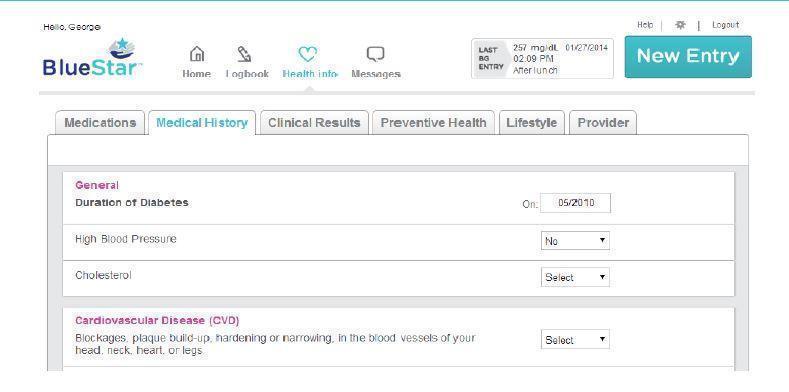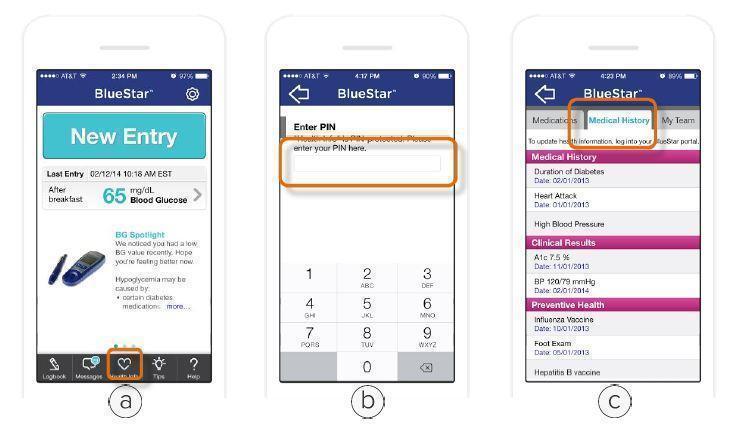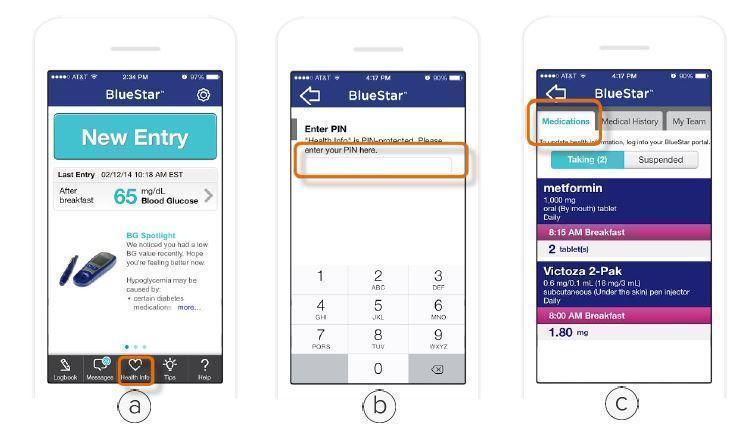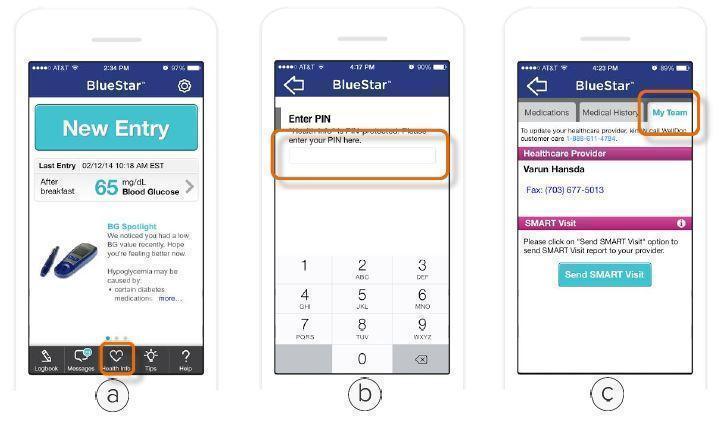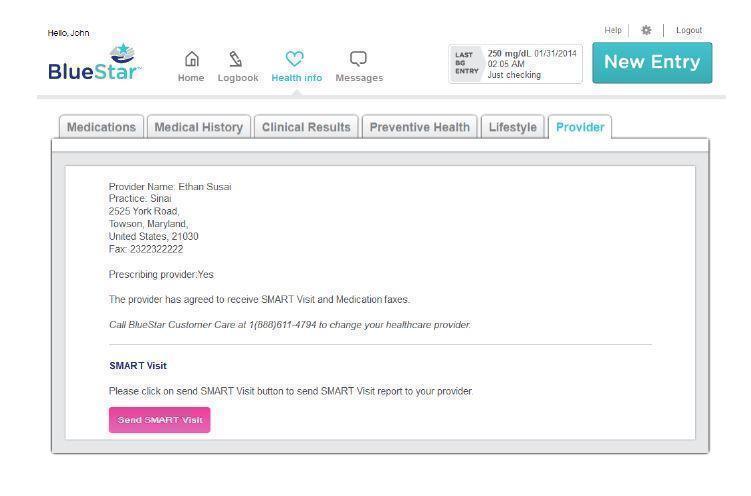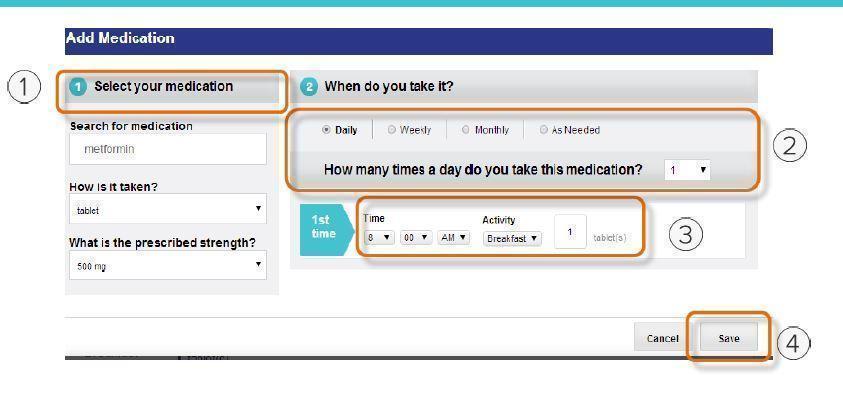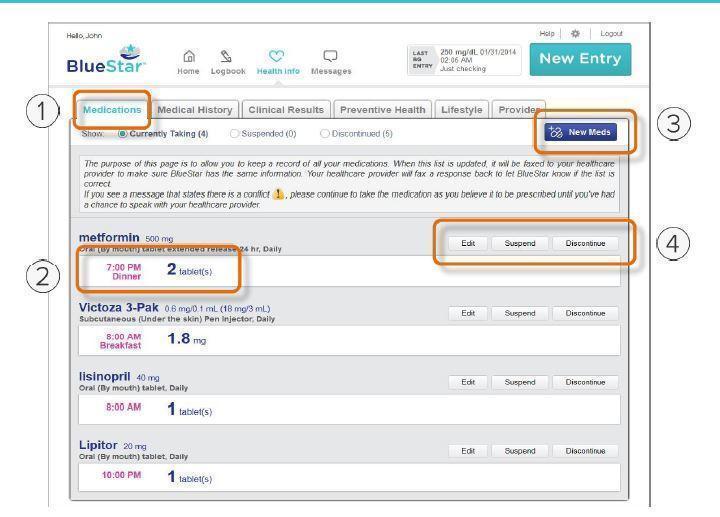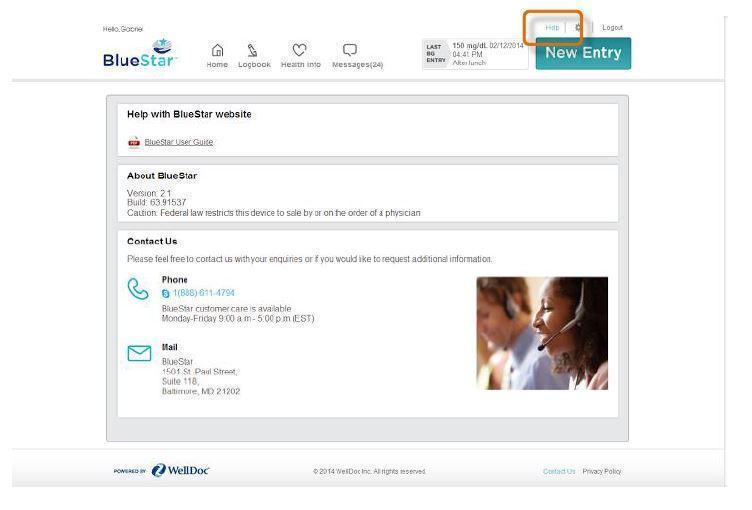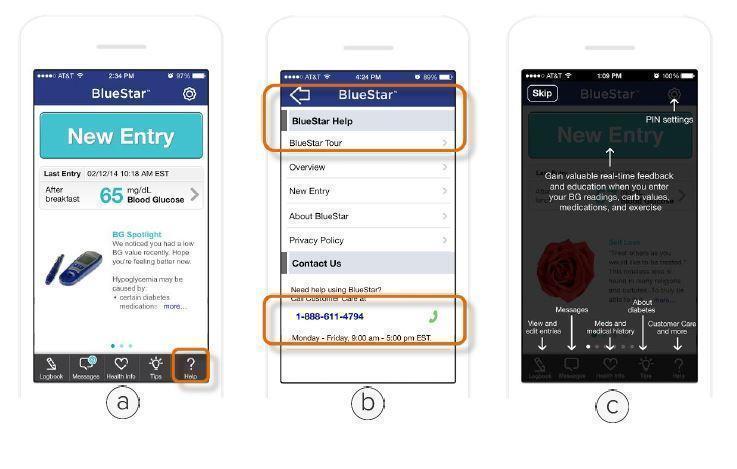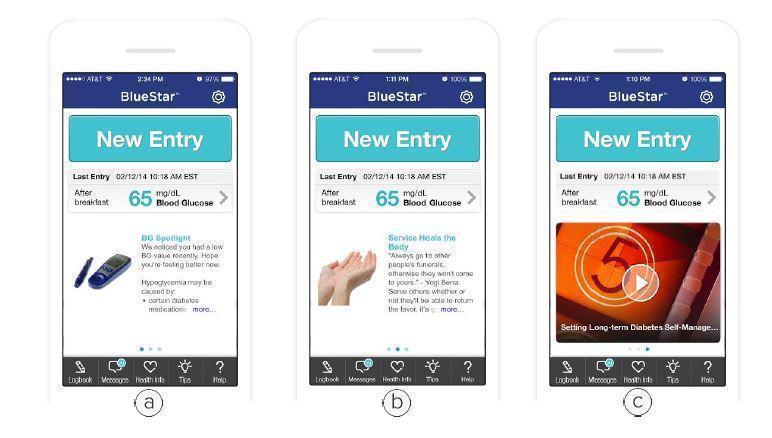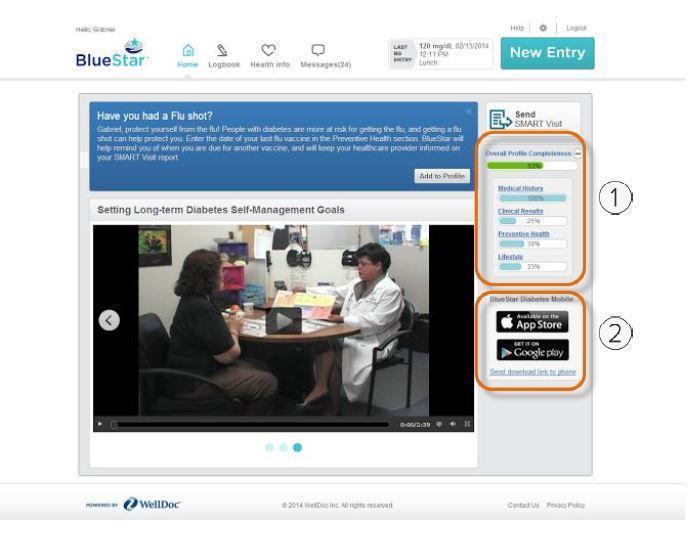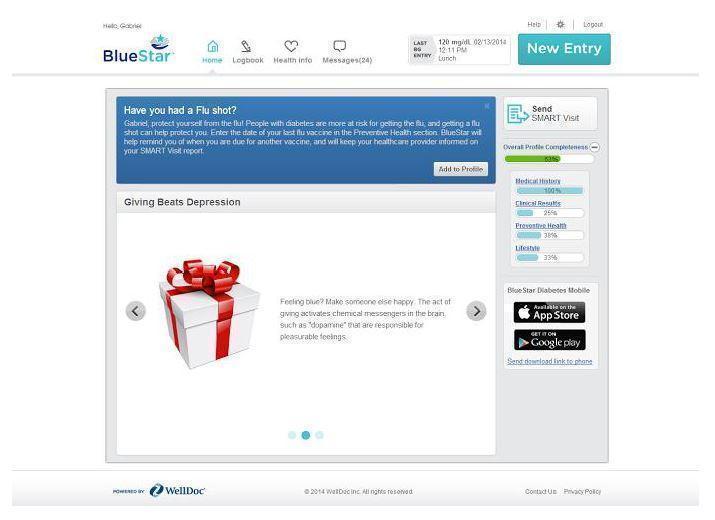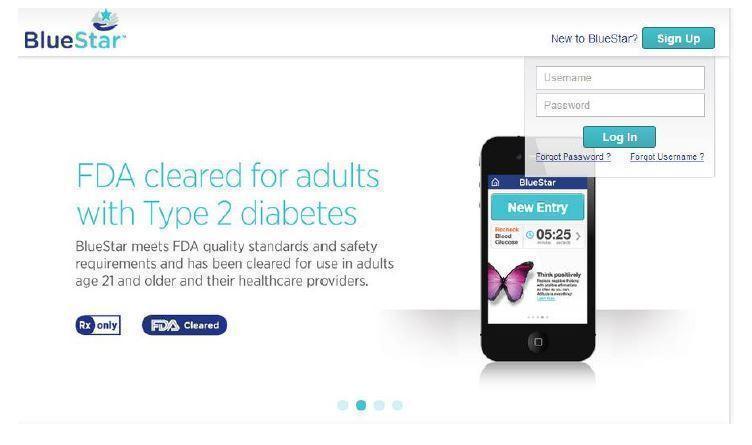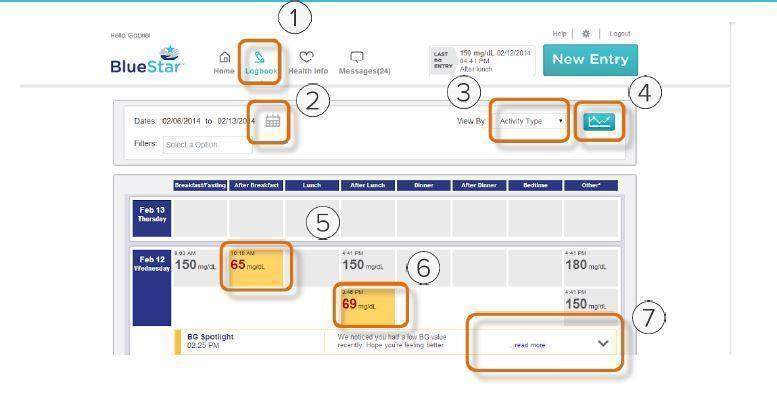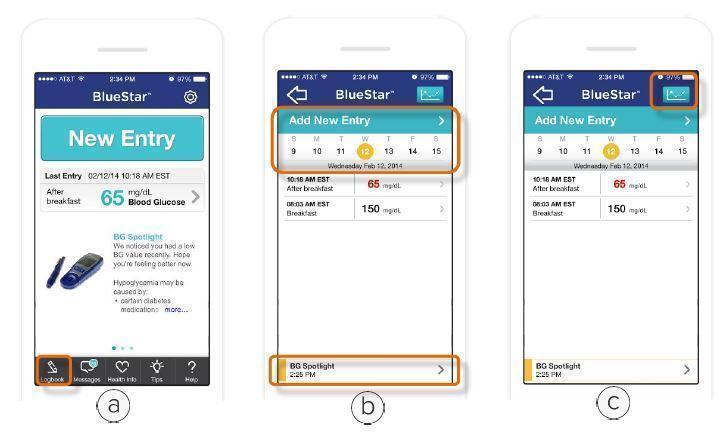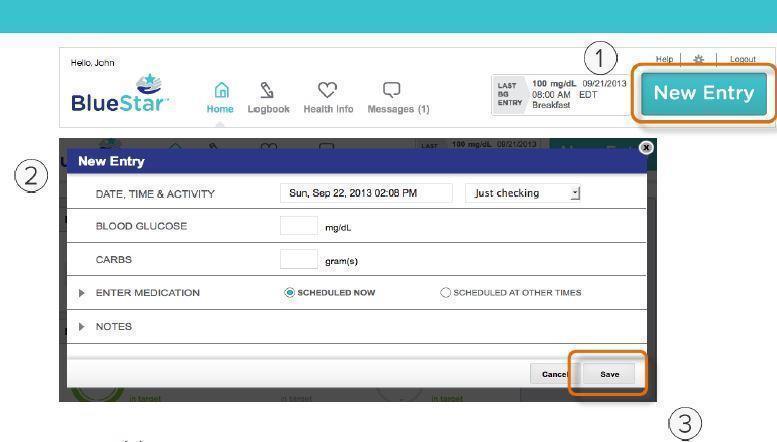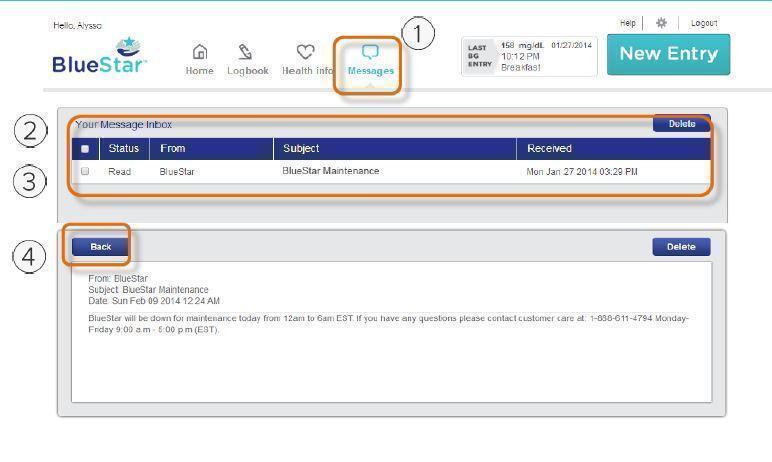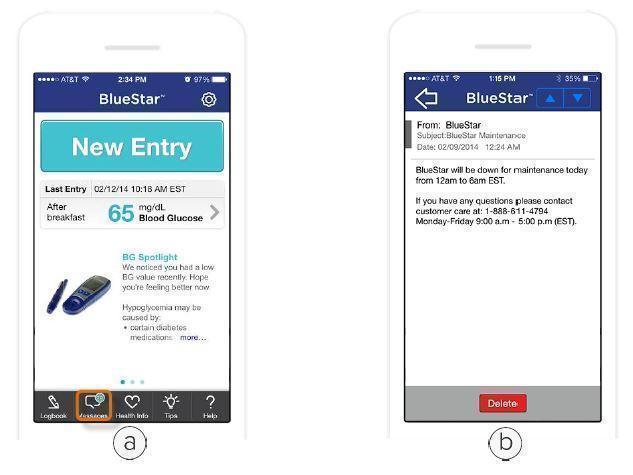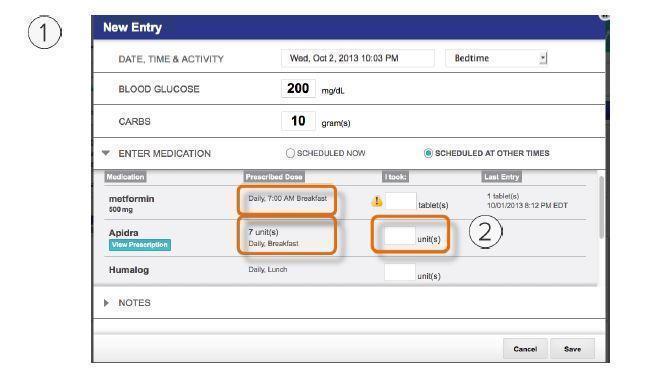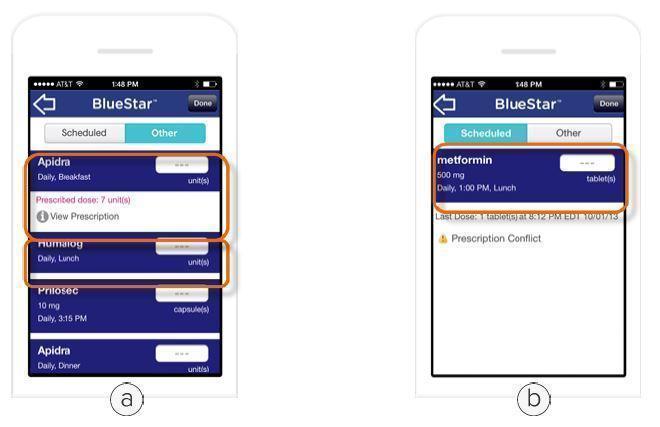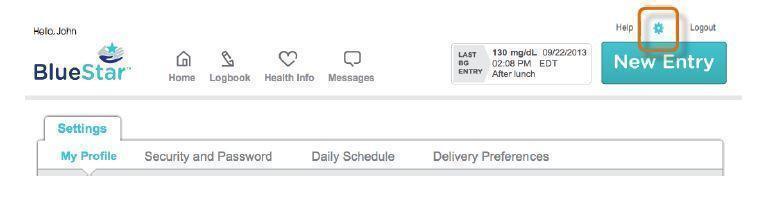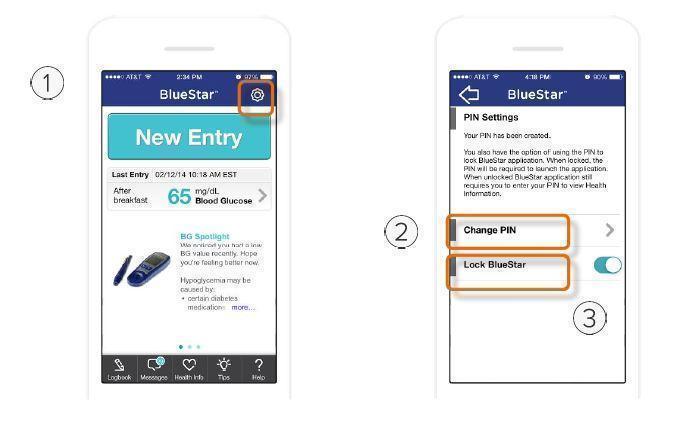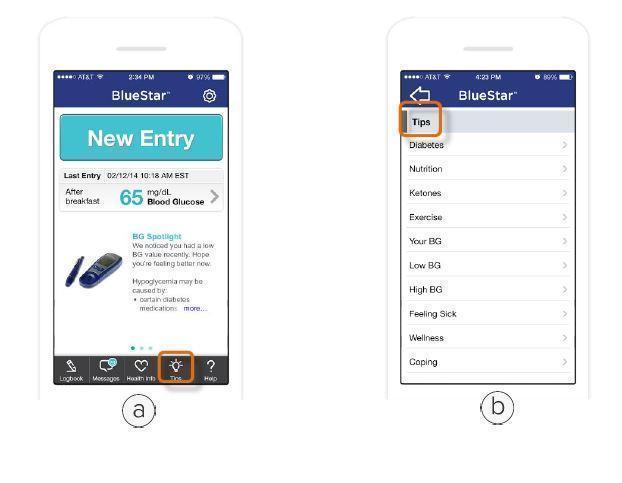 DRUG LABEL: WellDoc BlueStar or WellDoc DiabetesManager System and DiabetesManager Rx System
NDC: 89129-0100-01
Manufacturer: WellDoc, Inc
Category: other | Type: MEDICAL DEVICE
Date: 20140326

Prescription Medical Device

User Guide

WellDoc BlueStar or WellDoc DiabetesManager® System and DiabetesManager®-RxSystem Registration and Listing

WellDoc BlueStar (NDC/NHRIC #89129-0100-01) is an FDA cleared prescription product for adults with type 2 diabetes and their healthcare providers. BlueStar is registered in the FDA “Establishment Registration & Device Listing” database of FDA cleared products. For clarity, the product was originally cleared under the trade name DiabetesManager® System and DiabetesManager®-RxSystem [Premarket Notification Numbers K100066, K112370, K120314] . Subsequently to the original clearance and prior to commercial launch, the BlueStar name was added to the device listing [as evidenced by the image below]

Product Description

The World’s First Mobile Prescription Therapy

BlueStar™ is an FDA Cleared product for type 2 diabetes. It is only available with a prescription from your healthcare provider.

IS BLUESTAR RIGHT FOR YOU?
Are you struggling to manage your diabetes? Is it overwhelming and confusing? We know that trying to remember your doctor’s
advice about medications, diet, and exercise isn’t easy, but diabetes doesn’t have to take over your life. Talk to your doctor about
getting a prescription for BlueStar.

DIABETES SUPPORT, ANYTIME ANYWHERE™
BlueStar is not a pill or a shot — it's a completely new kind of approach to support you and help you manage your type 2
diabetes. BlueStar’s real-time coaching fits into your daily life helping you stay on track with your diabetes self-care. It works with
you, struggles with you, achieves with you, and celebrates with you. It can help make living with diabetes easier which makes for
a healthier, happier you.
BlueStar is accessible from your mobile phone, tablet, or computer, and supports your healthcare provider’s instructions while
providing you with diabetes education and motivational support.

COORDINATE YOUR CARE WITH YOUR DOCTOR
Before your next diabetes check-up, you can use BlueStar to send your information to your doctor. This helps your healthcare
provider understand the challenges that you face between appointments so that during your office visit you can discuss a
treatment plan that is just right for you.

INDICATION FOR USE
BlueStar is indicated for use by healthcare providers and their adult patients, aged 21 years and older, who have type 2 diabetes.
BlueStar provides secure capture, storage, and transmission of diabetes data, as well as, motivational, behavioral, and
educational coaching messages to aid in diabetes self-management. BlueStar is not intended to replace the care provided by a
licensed healthcare professional, including prescriptions, diagnosis, or treatment.

CONTRAINDICATIONS: Type 1 diabetes, patients on insulin pumps, patients less than 21 years of age, and women who are
pregnant.

IMPORTANT SAFETY INFORMATION: For medical questions, please contact your healthcare provider. If you are experiencing an
emergency, please dial 911.

Caution: Federal law restricts this device to sale by or on the order of a physician.

For more information visit www.bluestardiabetes.com

BlueStar Customer Care

Available to Answer Your Questions

BlueStar™ Customer Care can assist you with the following:
• How to use BlueStar
• Reporting of errors when trying to use BlueStar
• Technical questions related to BlueStar on web and/or mobile
• Questions about your prescription or health insurance reimbursement

Available: Monday-Friday, 9:00 a.m.-5:00 p.m. (ET)
Phone: (888) 611-4794

Getting Started

If you are new to BlueStar™, select the Sign Up button to begin the registration process or Log In with your username and password.

Getting Started...Continued

Enter your Prescription Number, BlueStar™ ID, and personal information to create your BlueStar account.

Using BlueStar on your phone

BlueStar™ on mobile is recommended for use on phones with iOS 6 and greater or Android OS 2.2 and greater

BlueStar Mobile

Log In
a. Enter Username.
b. Enter Password.
c. Tap Log In.

Trouble logging in?
d. Tap Forgot Password? to retrieve your BlueStar™ password.
e. Tap Forgot Username? to retrieve your BlueStar username.

New to BlueStar?
f. Tap Sign Up to register for BlueStar. This will prompt you to complete your registration via the registration form.

Home Screen (Mobile)

The BlueStar™ carousel displays important information to help you manage your diabetes.

a. BG Spotlight. Your BG entries are reviewed on a daily basis. When BlueStar sees something worth noting, it delivers a message to your carousel. The message also appears in your logbook for that day.

b. Motivational Message. This provides support for your general health and well-being. A new motivational message is displayed daily.

c. Educational Video. The educational videos are designed to provide “need to know” information about diabetes in a way that fits into your busy schedule. The videos are short (2-5 minutes) and cover various aspects of diabetes. Each video is available for 48 hours before it is replaced by the next video in the carousel.

Entering Information

a. Click on New Entry.

b. Enter any of the following:
• Blood Glucose readings (BG)
• Number of Carbs in your meal
• Medication - Medications are displayed as “Scheduled” or “Other”. Daily medications are displayed under “Scheduled” if their administration time is within 60 minutes of the current time. Weekly and Monthly medications are displayed under “Scheduled” if their administration time is within 8 hours of the current time. Medications that are not scheduled for the current time are displayed under “Other”.
• Notes - Tap Notes to enter important information related to your BG entry.

c. Activity Type - The Activity Type defaults according to your Daily Schedule presets on the web application. Scroll through to select your current Activity Type.

d. Date and Time - The current Date and Time is displayed. You may also adjust this portion to view or edit entries from an earlier date.

Recording Medications

a. Medication Administration Display:
• Your medications are displayed grouping your doses by the time of day you are scheduled to take them.
• Full prescription information for metabolic meds (those for BG, BP, or cholesterol) is only displayed once your provider confirms the dose (e.g. number of pills, units of insulin, etc.). If the dose is not yet confirmed, or there is a conflict between the information entered and your provider’s records, the name of the med will be displayed without the dose.
Note: Always continue your medications as prescribed and confirm your prescription information with your healthcare provider at your earliest convenience.
• For non-metabolic medications, we do not request that your provider confirm that information, so the total prescribed dose is never displayed.

b. Recording Your Medication Dose:
• Simply choose the medication you wish to record and enter the dose (number of pills, units of insulin, etc.) that you took.

Coaching Messages

BlueStar™ provides you with coaching messages about BGs within 120 minutes of the blood glucose entry (within 30 minutes if the blood glucose is less that 70 mg/dL). These messages provide you with several different types of information:
• Immediate coaching on your BG value
• Information on nutrition
• Education about diabetes related health issues like blood pressure and cholesterol
• Messages of motivation and inspiration, or personal stories from other people with diabetes
All BGs entered are included in the BG Spotlight message if the BG shows something important that you should pay attention to.

Messages

The number displayed over the Messages Icon indicates the number of unread messages in your Inbox.

a. Tap on Messages.
b. Tap on the message you wish to view. Tap the Back Arrow to return to the list of messages or Delete to remove the message from your Inbox.

Note: Your BlueStar™ messaging system is a read-only system. You cannot send or forward messages from it.

Logbook

Logbook is a record of all your BG readings and related information such as carbs, meds, and notes entered into the BlueStar™ system.

a. Tap on the Logbook icon.
b. Select a date and Add New Entry to enter current or earlier information. You can also tap to view the BG Spotlight for that day if available.
c. Tap the Graph icon to view a trend chart of your entries.

Note: Only the last thirty (30) days of data will appear in the logbook on your phone. You can edit any logbook entry, simply by clicking on it, making changes and saving it. To view your complete logbook display or to print, please Log In to the BlueStar website.

Health Info: (Medications)

This is where you can review all your medication information. To add or change medications, please log into www.bluestardiabetes.com
a. Tap on Health Info.
b. Enter your PIN. If you have not created a PIN, BlueStar™ will prompt you to create one.
c. Tap on Medications to view the medications you have entered into BlueStar.

Note: Health Information cannot be added or edited on your phone. To edit your Health Information log on to www.bluestardiabetes.com

IMPORTANT SAFETY INFORMATION:
For medical questions, please contact your healthcare provider. If you are experiencing an emergency, please dial 911.

Health Info: (Medical History)

This is where you can review your medical history, lab results and preventive health information. To add or change medical history, please log in at www.bluestardiabetes.com

a. Tap on Health Info.
b. Enter your PIN. If you have not created a PIN, BlueStar™ will prompt you to create one.
c. Tap the Medical History tab to view information that you have entered into BlueStar.

Note: Health Information cannot be added or edited on your phone. To edit your Health Information log on to www.bluestardiabetes.com

Health Info: (My Team)

This is where you can review your healthcare provider information and send a SMART Visit to your healthcare provider. To make changes to your healthcare provider information, you must call BlueStar™ Customer Care at (888) 611-4794. Available: Monday-Friday, 9:00 a.m.-5:00 p.m. (ET).

a. Tap on Health Info.
b. Enter your PIN. If you have not created a PIN, BlueStar will prompt you to create one.
c. Tap the My Team tab to view your provider information.

Note: SMART Visit is a report containing your lab results, dates of screening exams and vaccinations, logbook entries, and medication list. It is suggested that you send SMART Visit 1-2 days prior to an office visit so that your healthcare provider will have it to review with you at that time.

Settings

1. PIN Settings
Use PIN Settings to change your PIN number or lock BlueStar™. A PIN is required to access your Health Info.
• Tap on the Cog icon.

2. Change PIN
• Tap on Change PIN.
• Enter your current PIN and then your new PIN number.

3. Lock BlueStar
• Move the Lock BlueStar slider control to the right to lock your application.

Tips

a. Tap on Tips.
b. Tap on each Tips category to view information to help you understand and manage your diabetes better.

Help

There are two ways to access helpful information about BlueStar™ from your phone:

a. Tap on the Help icon.

b. BlueStar Help
• Tap on BlueStar Tour to take a tour of BlueStar.
• Tap the Help categories to view helpful information.
• Tap the Customer Care number to speak with a BlueStar customer care representative. Available: Monday-Friday, 9:00 a.m.-5:00 p.m. (ET).

c. BlueStar Tour

Using BlueStar on the Web

Note: BlueStar™ on web is recommended for use on computers with Internet Explorer 10 and 11 and Mozilla Firefox 25 and 26 and Chrome 32

Log In

a. Enter Username.
b. Enter Password.
c. Click Log In.

Trouble logging in?
d. Click Forgot Password to retrieve your BlueStar™ password.
e. Click Forgot Username to retrieve your BlueStar username.

New to BlueStar?
a. Click Sign Up to register for BlueStar.

Home Screen (Web)

The BlueStar™ carousel displays important information to help you manage your diabetes.

• BG Spotlight. Your BG entries are reviewed on a daily basis. When BlueStar sees something worth noting, it delivers a message to your carousel. The message also appears in your logbook for that day.

• Motivational Message. This provides support for your general health and well-being. A new motivational message is displayed daily.

• Educational Video. The educational videos are designed to provide “need to know” information about diabetes in a way that fits into your busy schedule. The videos are short (2-5 minutes) and cover various aspects of diabetes. Each video is available for 48 hours before it is replaced by the next video in the carousel.

Home Screen (web) Continued

1. Profile Complete: This is a display of the status of the completion of your overall Health Info profile and each individual section. Clicking on any of the links will directly take you to the respective section. Alternatively you can click on Health Info to complete your profile.
Note: Entering Clinical Results, Preventive Health, Medical History, and Lifestyle information will help customize BlueStar™ for you.

2. Download the BlueStar app: Click on the link to receive an SMS to download BlueStar. You can also download the BlueStar app via Google Play or the iTunes App Store.

Making Entries (Web)

1. Click on New Entry.

2. Enter your data.
a. Select the Date and Time. Note: Will default to current date and time.
b. Select the Activity (Breakfast, Fasting, Bedtime, etc.) Note: Will default to an activity based on the Daily Schedule.
c. Enter your Blood Glucose reading (BG).
d. Enter your Carbs (if applicable).
e. Medication - Medications are displayed as “Scheduled Now” or “Scheduled at Other Times”. Daily medications are displayed under “Scheduled Now” if their administration time is within 60 minutes of the current time. Weekly and Monthly medications are displayed under “Scheduled Now” if their administration time is within 8 hours of the current time. Medications that are not scheduled for the current time are displayed under “Scheduled at Other Times”.
f. Notes - Enter any applicable notes. (Up to 6 multiple choice items or type in your own).

3. Click on Save.

Recording Medications (Web)

1. Medication Administration Display:
a. Your medications will be displayed grouping your doses by the time of day you are scheduled to take them.
b. For metabolic medications (those for blood glucose, blood pressure, or cholesterol), the full prescription information will be displayed once your provider confirms the dose. If the information has not yet been confirmed, or if there is a conflict between the information you
entered and your provider’s records, the name of the medication will be displayed without the prescribed dose (e.g. number of pills, units of insulin, etc.)
c. For non-metabolic medications, we do not request that your provider confirm that information, so the total prescribed dose is never displayed.
Note: Always continue to take your medications as prescribed and confirm your prescription information with your healthcare provider at your earliest convenience.

2. Recording your Medication Dose:
a. Simply choose the medication you wish to record and enter the dose (number of pills, units of insulin, etc.) that you took.

Coaching Messages (Web)

BlueStar™ provides you with coaching messages about BGs within 120 minutes of the blood glucose entry (within 30 minutes if the blood glucose is less that 70 mg/dL). These messages provide you with several different types of information:

• Immediate coaching on your BG value
• Information on nutrition
• Education about diabetes related health issues like blood pressure and cholesterol
• Messages of motivation and inspiration, or personal stories from other people with diabetes

All BGs entered are in the BG Spotlight message if the BG shows something important that you should pay attention to.

Messages (Web)

1. Click on Messages.
2. Review the list of messages.
3. Click on the message you wish to read.
4. Click on Back to return to the list of messages or Delete to remove the message from your Inbox.

Note: Your BlueStar™ messaging system is a read-only system. You cannot send or forward messages from it

Logbook (Web)

Logbook is a record of all your BG readings and related information (carbs, meds, notes,) entered into the BlueStar™ system.
1. Click on Logbook.
2. Click on the Calendar icon to customize the date range.
3. Click on View By dropdown to change the view to view by time.
4. Click on the Graph icon to view Logbook as a graph.
5. You can edit any Logbook entry by clicking on it, making changes and saving it.
6. You can also add historical entries to the Logbook by clicking inside of a cell.
7. Click on Arrow to view BG Spotlight.

Health Info (Medications) (Web)

1. Medications: This is where you can manage your medications in BlueStar™.

2. Complete prescription information is displayed including:
a. Name, Strength, Dose Time, associated Activity and Dose Amount
Note: For medications that need to be taken with food such as short-acting insulin’s (including those in combination with other types of insulin), and certain oral medications such as sulfonylureas and metaglinides, only the associated meal type is displayed with the dose and not a time.

3. Click on New Meds to add a medication.

4. Edit/Suspend/Discontinue.
a. Click Edit to change a medication dose or time.
b. Click Suspend to temporarily stop a medication.
c. Click Discontinue to permanently stop a medication.

IMPORTANT SAFETY INFORMATION:
For medical questions, please contact your healthcare provider. If you are experiencing an emergency, please dial 911.

Health Info (Medications) (Web) (continued)

Adding New Meds: Once you have selected New Meds from the medication display screen (Step 3 on the previous page), you can enter new medication information.

1. Select the medication name, how it is taken (i.e. tablet, injection, etc.) and prescribed strength (i.e. how many mg or units).
2. Select whether you take it daily, weekly, monthly, or as needed. Then select how many times per day, week, month, etc. you take it.
3. Select the time that you take your medication and the associated activity (e.g. 8:00 A.M., breakfast). Enter your dose (number of pills, units, etc.) at each administration time. If you take the medication more than once per day, week, month, etc., the appropriate
number of times will appear.
4. Click Save.

Health Info (Medical History, Clinical Results etc.) (Web)

Use this section to record your important health information into BlueStar™, incuding:
1. Medical History (other medical problems that can affect your diabetes management).
2. Clinical Results (A1C, cholesterol, kidney function tests, etc.).
3. Preventive Health (vaccinations, foot exam, eye exam, etc.).
4. Lifestyle information (height, weight, smoking history).
Note: If you’re not sure of the answer to some of the questions, be sure to discuss it with your healthcare provider. Remember to update your information periodically.

Health Info (Provider) (Web)

This is where you can review your healthcare provider information and send a SMART Visit to your healthcare provider.
To make changes to your healthcare provider information, you must call BlueStar™ Customer Care at (888) 611-4794. Available: Monday-Friday, 9:00 a.m.-5:00 p.m. (ET).

Note: SMART Visit is a report containing your Logbook entries, Medication list, and a summary of your Medical History. It is suggested that you send SMART Visit 1-2 days prior to an office visit so that your healthcare provider will have it to review with you at that time.

Settings (Web)

Click on the Cog icon to make updates to your settings.
• My Profile: Email Address
Note: No changes can be made after registration to basic profile information. If you have changed your name due to marriage, divorce or other legal means, please call customer care.
• Security and Password: User Name, Password, Security Questions
• Daily Schedule: Breakfast, Lunch, Dinner, Bedtime Schedules
• Delivery Preferences: Feedback Messaging, Email Reminders

Help (Web)

This is where you can download PDF information for using BlueStar™ and access contact information.